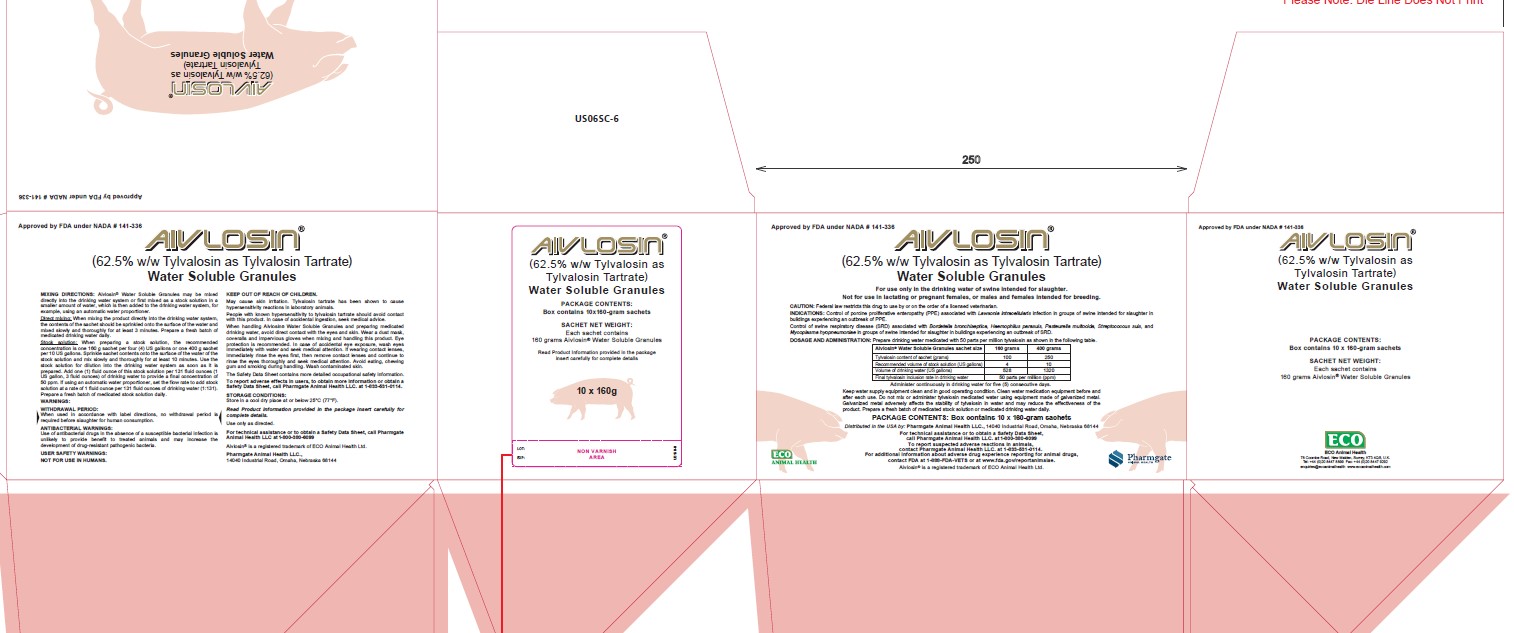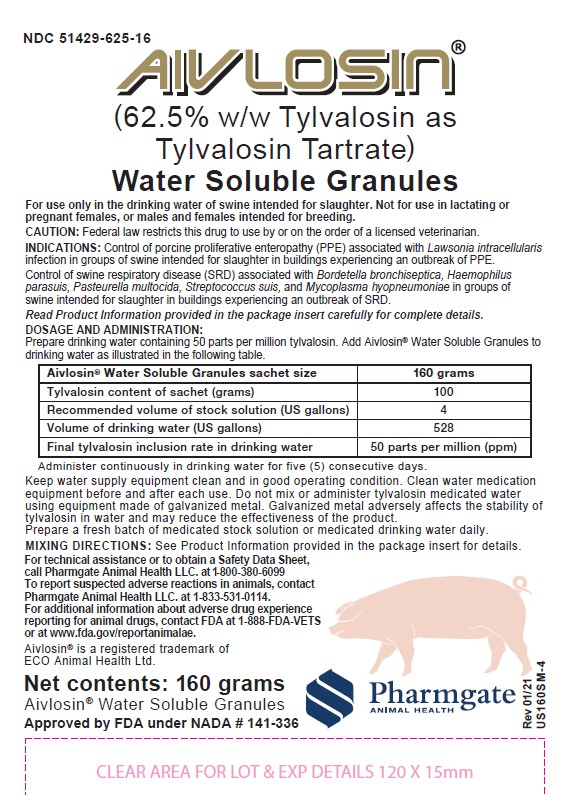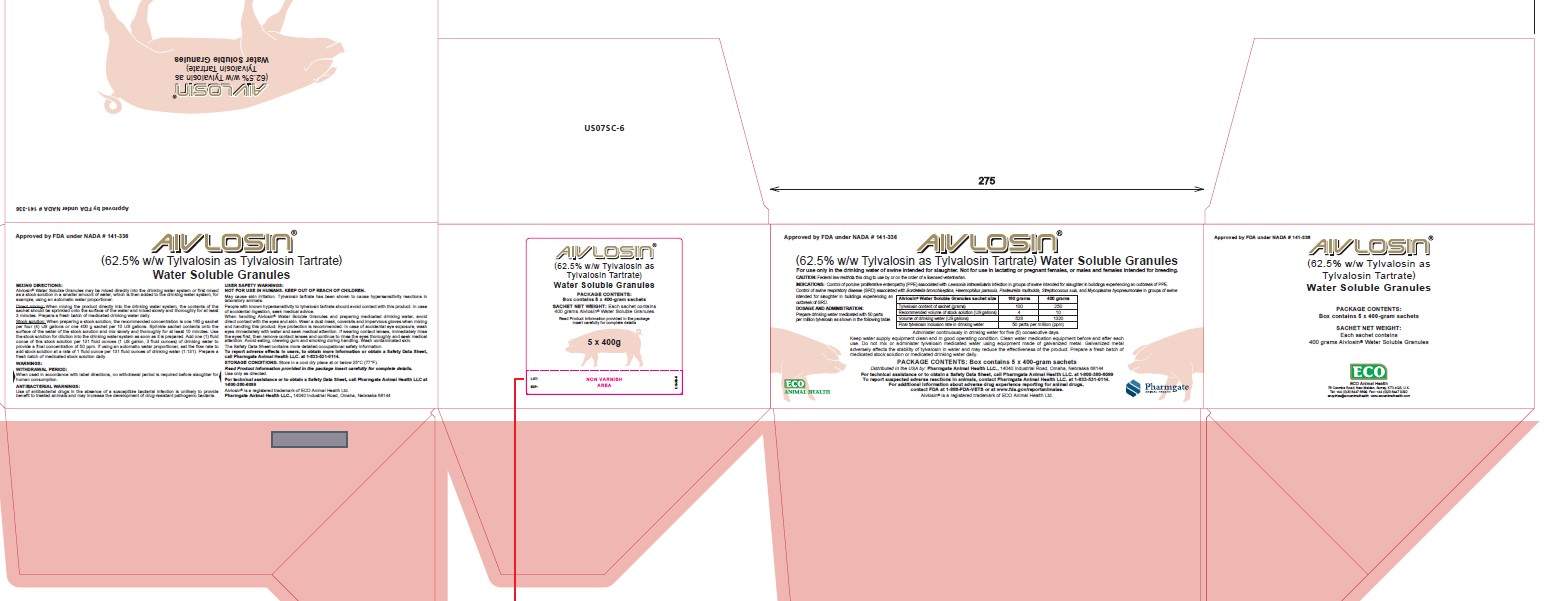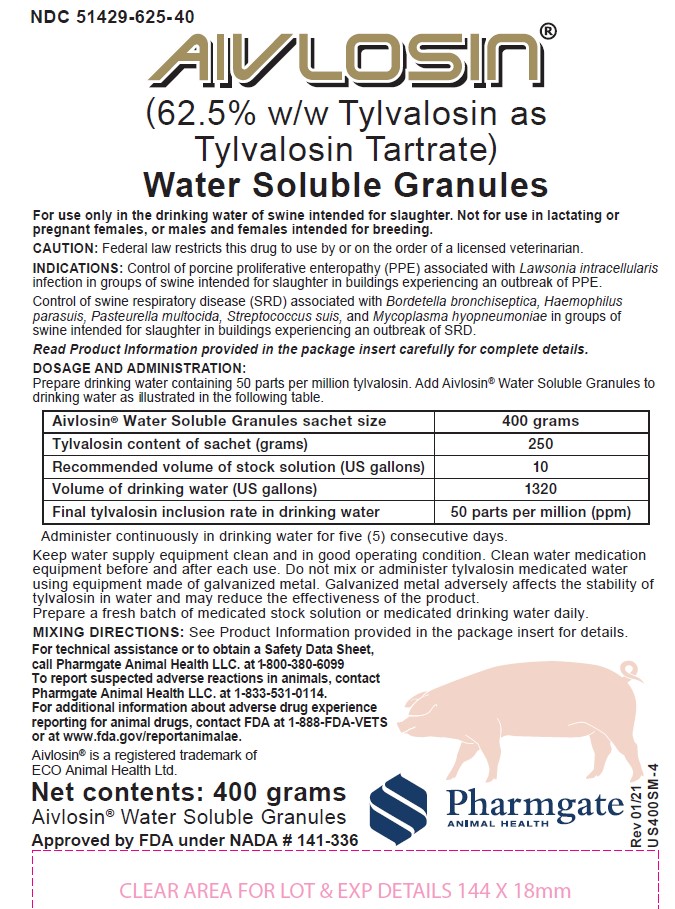 DRUG LABEL: Aivlosin
NDC: 51429-625 | Form: GRANULE, FOR SOLUTION
Manufacturer: Pharmgate Animal Health LLC
Category: animal | Type: PRESCRIPTION ANIMAL DRUG LABEL
Date: 20211129

ACTIVE INGREDIENTS: Tylvalosin tartrate 62.5 g/100 g
INACTIVE INGREDIENTS: Lactose monohydrate

Approved by FDA under NADA # 141-336

AIVLOSIN®

(62.5% w/w Tylvalosin as Tylvalosin Tartrate)

Water Soluble Granules

For use only in the drinking water of swine intended for slaughter.

Not for use in lactating or pregnant females, or males and females intended for breeding.

CAUTION:

Federal law restricts this drug to use by or on the order of a licensed veterinarian.

PRODUCT DESCRIPTION:

Aivlosin® (Tylvalosin Tartrate) Water Soluble Granules is a water soluble granular powder for oral use by administration in the drinking water. Each gram of Aivlosin® Water Soluble Granules contains 0.625 grams of tylvalosin as tylvalosin tartrate.

ANTIBIOTIC CLASSIFICATION:
Tylvalosin, the active ingredient in Aivlosin® Water Soluble Granules, is a macrolide antibiotic.

INDICATIONS:

Control of porcine proliferative enteropathy (PPE) associated with Lawsonia intracellularis infection in groups of swine in buildings experiencing an outbreak of PPE.

Control of swine respiratory disease (SRD) associated with Bordetella bronchiseptica, Haemophilus parasuis, Pasteurella multocida, Streptococcus suis, and Mycoplasma hyopneumoniae in groups of swine intended for slaughter in buildings experiencing an outbreak of SRD.

DOSAGE AND ADMINISTRATION:

Prepare drinking water medicated with 50 parts per million Tylvalosin as shown in the following table.

Aivlosin® Water Soluble Granules sachet size | 160 grams | 400 grams
Tylvalosin content of sachet (grams) | 100 | 250
Recommended volume of stock solution (US gallons) | 4 | 10
Volume of drinking water (US gallons) | 528 | 1320
Final tylvalosin inclusion rate in drinking water | 50 parts per million (ppm)

Administer continuously in drinking water for five (5) consecutive days.

Keep water supply equipment clean and in good operating condition. Clean water medication equipment before and after each use. Do not mix or administer Tylvalosin medicated water using equipment made of galvanized metal. Galvanized metal adversely affects the stability of Tylvalosin in water and may reduce the effectiveness of the product. Prepare a fresh batch of medicated stock solution or medicated drinking water daily.

MIXING DIRECTIONS:

Aivlosin® Water Soluble Granules may be mixed directly into the drinking water system or first mixed as a stock solution in a smaller amount of water, which is then added to the drinking water system, for example, using an automatic water proportioner.

Direct mixing:

When mixing the product directly into the drinking water system, the contents of the sachet should be sprinkled onto the surface of the water and mixed slowly and thoroughly for at least 3 minutes. Prepare a fresh batch of medicated drinking water daily.

Stock solution:

When preparing a stock solution, the recommended concentration is one 40-gram sachet per US gallon, or one 160-g sachet per four (4) US gallons or one 400-gram sachet per 10 US gallons. Sprinkle sachet contents onto the surface of the water of the stock solution and mix slowly and thoroughly for at least 10 minutes. Use the stock solution for dilution into the drinking water system as soon as it is prepared. Add one (1) fluid ounce of this stock solution per 131 fluid ounces (1 US gallon, 3 fluid ounces) of drinking water to provide a final concentration of 50 ppm. If using an automatic water proportioner, set the flow rate to add stock solution at a rate of 1 fluid ounce per 131 fluid ounces of drinking water (1:131). Prepare a fresh batch of medicated stock solution daily.

WARNINGS:

WITHDRAWAL PERIOD:

When used in accordance with label directions, no withdrawal period is required before slaughter for human consumption.

RESIDUE WARNING

ANTIBACTERIAL WARNINGS:

Use of antibacterial drugs in the absence of a susceptible bacterial infection is unlikely to provide benefit to treated animals and may increase the development of drug-resistant pathogenic bacteria.

USER SAFETY WARNINGS:

NOT FOR USE IN HUMANS.
KEEP OUT OF REACH OF CHILDREN.

May cause skin irritation. Tylvalosin Tartrate has been shown to cause hypersensitivity reactions in laboratory animals. People with known hypersensitivity to Tylvalosin Tartrate should avoid contact with this product. In case of accidental ingestion, seek medical advice.

When handling Aivlosin® Water Soluble Granules and preparing medicated drinking water, avoid direct contact with the eyes and skin. Wear a dust mask, coveralls and impervious gloves when mixing and handling this product. Eye protection is recommended. In case of accidental eye exposure, wash eyes immediately with water. If irritation persists, seek medical attention. Avoid eating, chewing gum and smoking during handling. Wash contaminated skin.

The Safety Data Sheet contains more detailed occupational safety information.

To report adverse effects in users, to obtain more information or obtain a Safety Data Sheet, call Pharmgate Animal Health LLC. at 1-833-531-0114.

PRECAUTIONS:

Not for use in lactating or pregnant females, or males and females intended for breeding. The effects of Tylvalosin on swine reproductive performance, pregnancy and lactation have not been determined. The safety and efficacy of this formulation in species other than swine have not been determined.

To assure both food safety and responsible use in swine, concurrent use of tylvalosin in medicated drinking water and tylvalosin or another macrolide in medicated feed or by any other route of administration should be avoided. Tylvalosin belongs to the macrolide antimicrobial drug class. Macrolides are ranked as a critically important drug in human medicine; therefore, minimizing the risk of development of antimicrobial resistance to this class of drug is very important. The following conditions of use and restrictions listed below are critical for
the FDA's strategy of risk management associated with tylvalosin:

Always treat the fewest number of animals necessary to control a respiratory disease or PPE outbreak.

Do not immediately follow this macrolide treatment with another macrolide treatment via any route.

Prescriptions should not be renewed or refilled for animals already treated with one course of therapy with tylvalosin asdirected (See Dosage and Administration above).

ADVERSE REACTIONS IN ANIMALS:

No adverse reactions related to the drug were observed during clinical or target animal safety trials. To report suspected adverse reactions in animals, contact Pharmgate Animal Health LLC. at 1-833-531-0114. For additional information about adverse drug experience reporting for animal drugs, contact FDA at 1-888-FDA-VETS or at www.fda.gov/reportanimalae.

CLINICAL PHARMACOLOGY:

Tylvalosin is a 16-membered semi-synthetic macrolide antibiotic. Macrolides are generally considered to be bacteriostatic agents that exert their antibiotic effect by reversibly binding to the 23S rRNA of the 50S ribosomal subunit, thereby inhibiting bacterial protein synthesis. The spectrum of activity of most available macrolides used in veterinary medicine is primarily against Gram-positive bacteria and Mycoplasmas, with some activity against Gram-negative fastidious bacteria. These compounds have no activity against the naturally resistant Enterobacteriaceae including Escherichia coli and Salmonella spp. Typically, macrolides achieve higher concentrations in tissues than in plasma.

EFFECTIVENESS:

Control of Porcine Proliferative Enteropathy (PPE):

A multi-location challenge model study was conducted to confirm the effectiveness of AIVLOSIN® Water Soluble Granules for the control of PPE associated with Lawsonia intracellularis. Pigs were challenged by intragastric gavage with a mucosal homogenate containing a North American isolate of Lawsonia intracellularis isolated in 2005 that induces representative disease in challenged pigs. When at least 15% of the study pigs were showing signs of infection based on abnormal fecal scores, pigs were provided water containing tylvalosin at an inclusion rate of 50 ppm for five consecutive days, or were provided non-medicated water. Effectiveness was evaluated using clinical scores (pig demeanor score, abdominal appearance score, and fecal score) and clinically-validated gross PPE lesion scores. A conclusion of the effectiveness of 50 ppm tylvalosin for the control of PPE was determined based on a statistically significant (p = 0.0103) improvement in the clinically-validated gross PPE lesion scores in the 50 ppm tylvalosin-treated group compared to the non-medicated group.

Control of Swine Respiratory Disease (SRD):

The effectiveness of Aivlosin® Water Soluble Granules for the control of swine respiratory disease (SRD) associated with Bordetella bronchiseptica, Haemophilus parasuis, Pasteurella multocida, Streptococcus suis and Mycoplasma hyopneumoniae was investigated in a natural field infection study conducted in the United States (three study sites) and Canada (one study site). Day 0 was defined when at least 15% of the candidate pigs were deemed clinically affected with SRD (moderate or severe respiratory score, moderate or severe
depression score, and rectal temperature greater than or equal to 104.0 °F). On Day 0 a total of 980 pigs were enrolled and randomly assigned to a tylvalosin-treated group (50 ppm tylvalosin in drinking water for 5 consecutive days) or a non-medicated control group. Treatment success was evaluated on Day 7 and was defined as a pig with normal or mild respiratory score, normal or mild depression score, and rectal temperature less than 104.0 °F. The proportion of pigs meeting the definition of treatment success was numerically higher in the tylvalosin-treated group (48.5%) compared to the proportion of pigs meeting the definition of treatment success in the non-medicated control group (41.6%), and the observed difference was statistically significant (p=0.0353).

Additional data to demonstrate the effectiveness of Aivlosin® Water Soluble Granules for the control of SRD associated with Mycoplasma hyopneumoniae was obtained in an experimentally-induced infection model study. Two hundred and forty (240) commercial crossbred pigs were challenged endotracheally with a representative isolate of M. hyopneumoniae. One hundred and ninety-two (192) study pigs were randomly assigned to either a tylvalosin-treated group (50 ppm tylvalosin in drinking water for 5 consecutive days) or a nonmedicated control group. Treatment was started when at least four of eight randomly pre-selected sentinel pigs exhibited a minimum of 3% weighted gross lung lesions consistent with M. hyopneumoniae infection. After a 5-day treatment period and a 5-day post-treatment period, study pigs were euthanized and necropsy performed to determine lung lesion scores. The analysis included 95 tylvalosin-treated pigs and 93 nonmedicated control pigs. There was a statistically significant (P<0.0001) improvement in pen mean M. hyopneumoniae lung lesion scores in the 50 ppm tylvalosin treated pigs (5.1%) compared to negative control (10.9%).

ANIMAL SAFETY:

Margin of safety:

Aivlosin® Water Soluble Granules given orally in drinking water at 0, 50, 150 and 250 ppm tylvalosin (0, 1×, 3× and 5× the labeled dose, respectively) to 8 healthy pigs per treatment group over 15 days (3× the labeled duration) did not result in drug-induced clinical signs, gross pathologic lesions, histopathologic lesions or clinically-relevant clinical pathology abnormalities.

STORAGE:

Store in a cool dry place at or below 25°C (77°F).

HOW SUPPLIED:

Aivlosin® Water Soluble Granules is packaged in 160- and 400-gram sachets supplied in boxes holding 10 and 5 sachets respectively.

LOT NO.: Printed on label.
EXPIRY: Printed on label.

Distributed in the USA by:
Pharmgate Animal Health LLC.
14040 Industrial Road,
Omaha, NE 68144
www.pharmgateah.com

For technical assistance or to obtain a Safety Data Sheet, call Pharmgate Animal Health LLC. at 1-800-380-6099

Aivlosin® is a registered trademark of ECO Animal Health Ltd.

PRINCIPAL DISPLAY PANEL - 160 g Packet and Carton

NDC 51429-625-16

AIVLOSIN®
(62.5% w/w Tylvalosin as
Tylvalosin Tartrate)
Water Soluble Granules

For use only in the drinking water of swine intended for slaughter. Not for use in lactating or pregnant females, or males and females intended for breeding.

CAUTION: Federal law restricts this drug to use by or on the order of a licensed veterinarian.

INDICATIONS: Control of porcine proliferative enteropathy (PPE) associated with Lawsonia intracellularis infection in groups of swine in buildings experiencing an outbreak of PPE.

Control of swine respiratory disease (SRD) associated with Bordetella bronchiseptica, Haemophilus parasuis, Pasteurella multocida, Streptococcus suis, and Mycoplasma hyopneumoniae in groups of swine intended for slaughter in buildings experiencing an outbreak of SRD.

Read Product Information provided in the package insert carefully for complete details.

DOSAGE AND ADMINISTRATION:Prepare drinking water containing 50 parts per million Tylvalosin. Add Aivlosin® Water Soluble Granules to drinking water as illustrated in the following table.

Aivlosin® Water Soluble Granules sachet size | 160 grams
Tylvalosin content of sachet (grams) | 100
Recommended volume of stock solution (US gallons) | 4
Volume of drinking water (US gallons) | 528
Final tylvalosin inclusion rate in drinking water | 50 parts per million (ppm)

Administer continuously in drinking water for five (5) consecutive days.

Keep water supply equipment clean and in good operating condition. Clean water medication equipment before and after each use. Do not mix or administer tylvalosin medicated water using equipment made of galvanized metal. Galvanized metal adversely affects the stability of tylvalosin in water and may reduce the effectiveness of the product.

Prepare a fresh batch of medicated stock solution or medicated drinking water daily.

MIXING DIRECTIONS: See Product Information provided in the package insert for details.

For technical assistance or to obtain a Safety Data Sheet, call Pharmgate Animal Health LLC. at 1-800-380-6099
To report suspected adverse reactions in animals, contact Pharmgate Animal Health LLC. at 1-833-531-0114.
For additional information about adverse drug experience reporting for animal drugs, contact FDA at 1-888-FDA-VETS or at www.fda.gov/reportanimalae.

Aivlosin® is a registered trademark of ECO Animal Health Ltd.

Net contents: 160 grams

Aivlosin® Water Soluble Granules

Approved by FDA under NADA # 141- 336

PharmGate
Animal Health

PACKAGE CONTENTS: Box contains 10 x 160-gram sachets

PRINCIPAL DISPLAY PANEL - 400 g Packet and Carton

NDC 51429-625-40

AIVLOSIN®
(62.5% w/w Tylvalosin as
Tylvalosin Tartrate)
Water Soluble Granules

For use only in the drinking water of swine intended for slaughter. Not for use in lactating or pregnant females, or males and females intended for breeding.

CAUTION: Federal law restricts this drug to use by or on the order of a licensed veterinarian.

INDICATIONS: Control of porcine proliferative enteropathy (PPE) associated with Lawsonia intracellularis infection in groups of swine in buildings experiencing an outbreak of PPE.

Control of swine respiratory disease (SRD) associated with Bordetella bronchiseptica, Haemophilus parasuis, Pasteurella multocida, Streptococcus suis, and Mycoplasma hyopneumoniae in groups of swine intended for slaughter in buildings experiencing an outbreak of SRD.

Read Product Information provided in the package insert carefully for complete details.

DOSAGE AND ADMINISTRATION:Prepare drinking water containing 50 parts per million Tylvalosin. Add Aivlosin® Water Soluble Granules to drinking water as illustrated in the following table.

Aivlosin® Water Soluble Granules sachet size | 400 grams
Tylvalosin content of sachet (grams) | 250
Recommended volume of stock solution (US gallons) | 10
Volume of drinking water (US gallons) | 1320
Final tylvalosin inclusion rate in drinking water | 50 parts per million (ppm)

Administer continuously in drinking water for five (5) consecutive days.

Keep water supply equipment clean and in good operating condition. Clean water medication equipment before and after each use. Do not mix or administer Tylvalosin medicated water using equipment made of galvanized metal. Galvanized metal adversely affects the stability of Tylvalosin in water and may reduce the effectiveness of the product.
Prepare a fresh batch of medicated stock solution or medicated drinking water daily.

MIXING DIRECTIONS: See Product Information provided in the package insert for details.

For technical assistance or to obtain a Safety Data Sheet, call Pharmgate Animal Health at 1-800-380-6099

To report suspected adverse reactions in animals, contact Pharmgate Animal Health LLC. at 1-833-531-0114.

For additional information about adverse drug experience reporting for animal drugs, contact FDA at 1-888-FDA-VETS
or at www.fda.gov/reportanimalae.

Aivlosin® is a registered trademark of

ECO Animal Health Ltd.

Net contents: 400 grams

Aivlosin® Water Soluble Granules

Approved by FDA under NADA # 141- 336

PharmGate
Animal Health

PACKAGE CONTENTS: Box contains 5 x 400-gram sachets